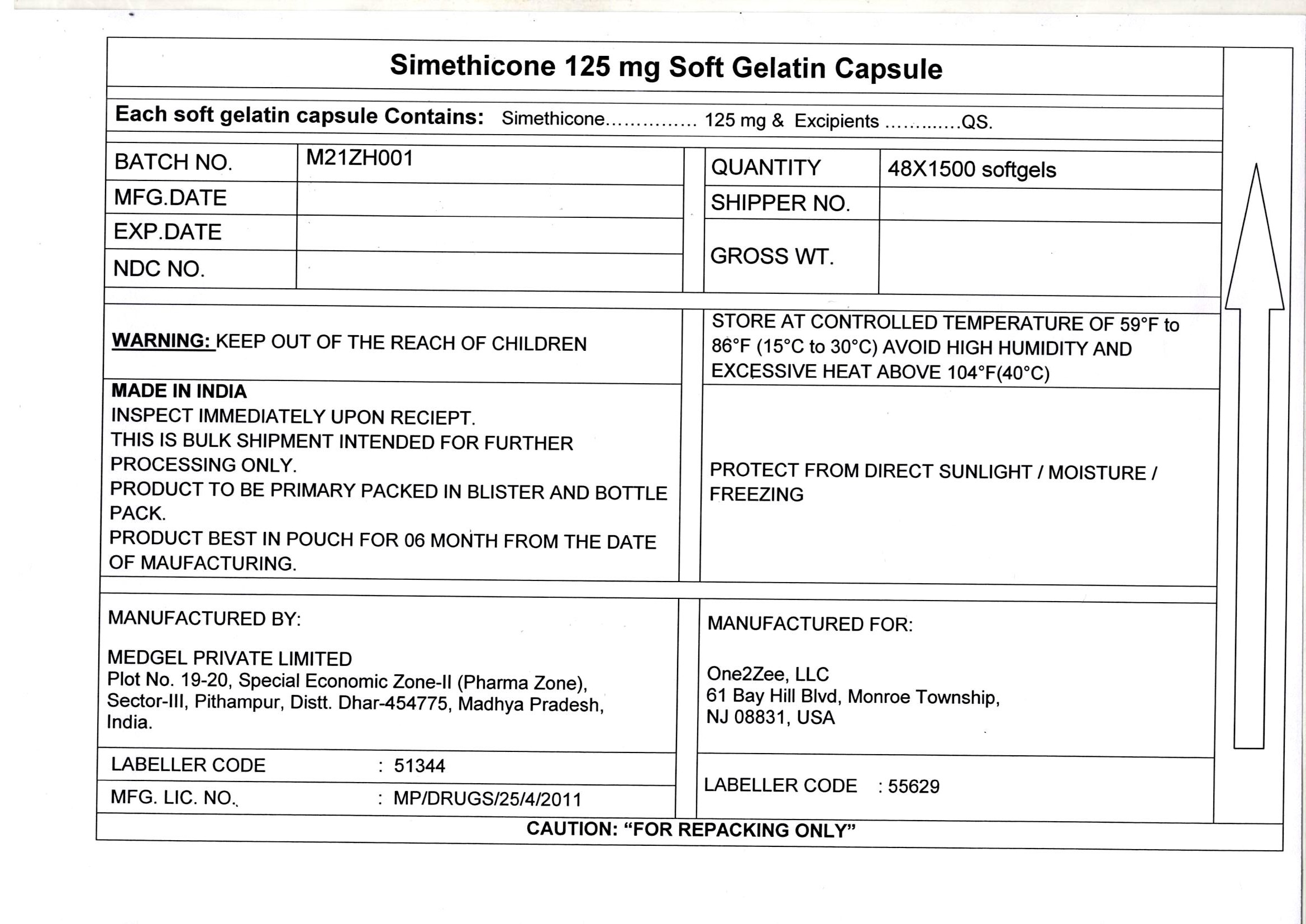 DRUG LABEL: Simethicone
NDC: 55629-010 | Form: CAPSULE, LIQUID FILLED
Manufacturer: ONE2ZEE LIMITED LIABILITY COMPANY
Category: otc | Type: HUMAN OTC DRUG LABEL
Date: 20230325

ACTIVE INGREDIENTS: DIMETHICONE 125 mg/1 1
INACTIVE INGREDIENTS: D&C YELLOW NO. 10; FD&C BLUE NO. 1; GELATIN; GLYCERIN; PEPPERMINT OIL; Povidone K30; SORBITOL; TITANIUM DIOXIDE; WATER

Extra Strength Gas Relief

Active ingredient (in each softgel)

Simethicone 125mg

Purpose

Antigas

Use

for the relief of

- pressure, bloating, and fullness commonly referred to as gas

Directions

- adults: swallow with water 1 or 2 softgels as needed after meals and at bedtime
- do not exceed 4 softgels in 24 hours except under the advice and supervision of a physician

Other Information

- store at controlled room temperature 20-25ºC (68-77ºF)
- protect from light, heat, and moisture

Inactive ingredients

FD&C blue 1, FD&C yello#10, gelatin, glycerin, peppermint oil, purified water, sorbitol sorbitan, titanium dioxide

PRINCIPAL DISPLAY PANEL - Shipping Label

IMETHICONE CAPSULES, 325 mg

Quantity : 48 Bags of 1500 Capsules each
NDC. No : 55629-010-01

Important:

1. Inspect immediately upon receipt

2. This is bulk shipment intended for further processing only

3. store at controlled room temperature 20-25ºC (68-77ºF), protect from light, heat, and moisture